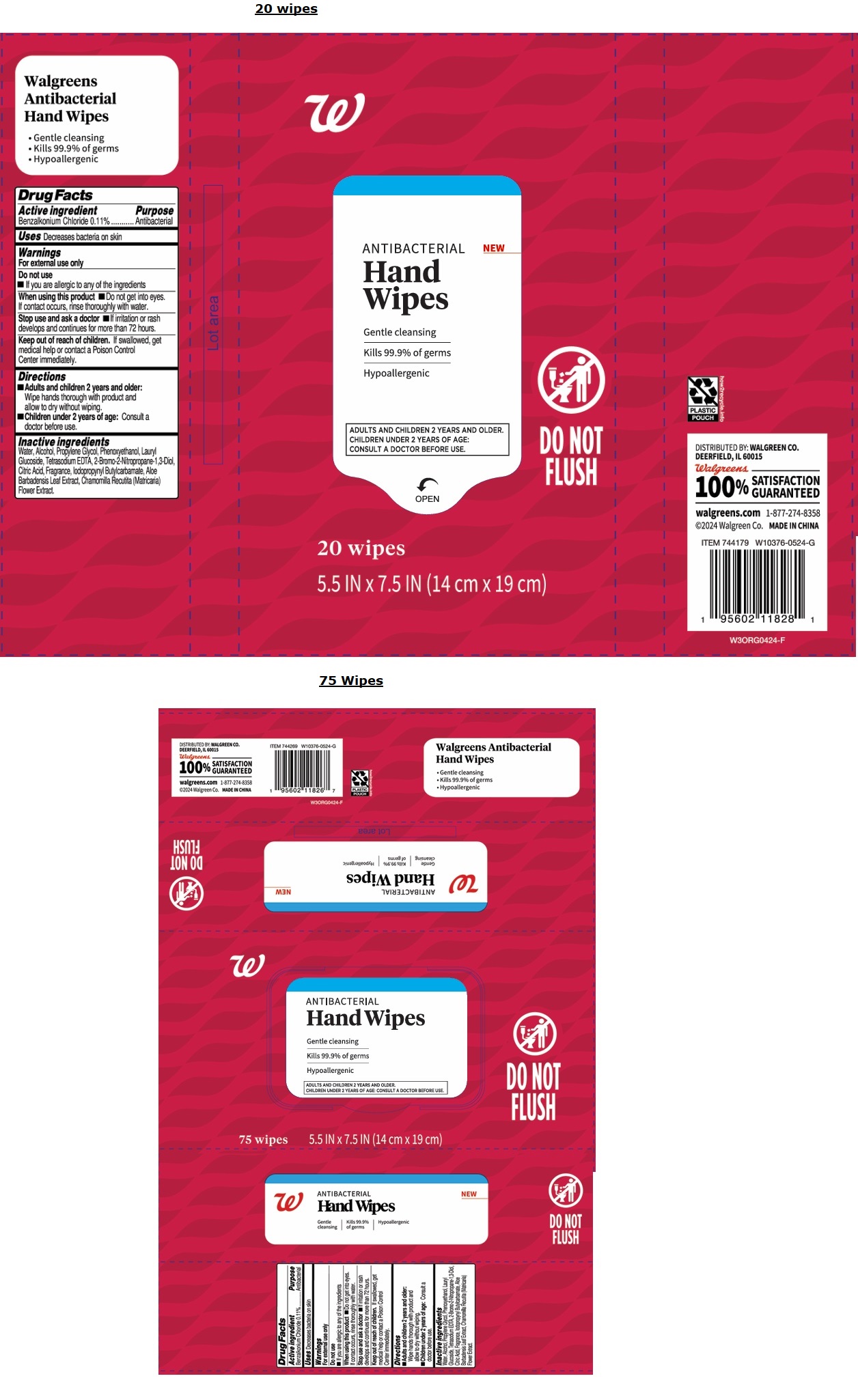 DRUG LABEL: Walgreens Antibacterial Hand Wipes
NDC: 0363-5189 | Form: CLOTH
Manufacturer: Walgreen Co.
Category: otc | Type: HUMAN OTC DRUG LABEL
Date: 20260115

ACTIVE INGREDIENTS: BENZALKONIUM CHLORIDE 0.11 g/100 mL
INACTIVE INGREDIENTS: WATER; ALCOHOL; PROPYLENE GLYCOL; PHENOXYETHANOL; LAURYL GLUCOSIDE; EDETATE SODIUM; BRONOPOL; CITRIC ACID MONOHYDRATE; IODOPROPYNYL BUTYLCARBAMATE; ALOE VERA LEAF; CHAMOMILE

Walgreens Antibacterial Hand Wipes

Active ingredient

Benzalkonium Chloride 0.11%

Purpose

Antibacterial

Uses

Decreases bacteria on skin

Warnings

For external use only

Do not use

•If you are allergic to any of the ingredients

When using this product •Do not get into eyes. If contact occurs, rinse thoroughly with water.

Stop use and ask a doctor •If irritation or rash develops and continues for more than 72 hours.

Keep out of reach of children. If swallowed, get medical help or contact a Poison Control Center immediately.

Directions

•Adults and children 2 years and older:

Wipe hands thorough with product and allow to dry without wiping.

•Children under 2 years of age: Consult a doctor before use.

Inactive ingredients

Water, Alcohol, Propylene Glycol, Phenoxyethanol, Lauryl Glucoside, Tetrasodium EDTA, 2-Bromo-2-Nitropropane-1,3-Diol, Citric Acid, Fragrance, Iodopropynyl Butylcarbamate, Aloe Barbadensis Leaf Extract, Chamomilla Recutita (Matricaria) Flower Extract.

Gentle cleansing

Kills 99.9% of germs

Hypoallergenic

DO NOT FLUSH

DISTRIBUTED BY: WALGREEN CO.

DEERFIELD, IL 60015

100% SATISFACTION GUARANTEED

walgreens.com 1-877-274-8358

©2024 Walgreen Co. MADE IN CHINA